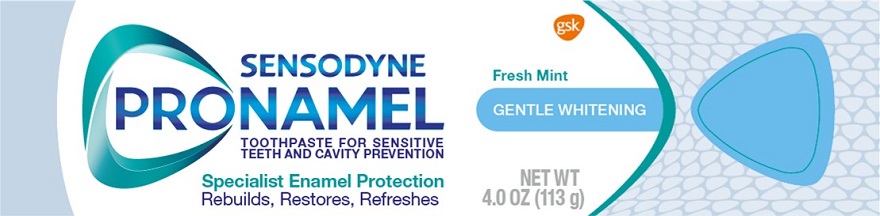 DRUG LABEL: Sensodyne Pronamel
NDC: 0135-0644 | Form: PASTE
Manufacturer: Haleon US Holdings LLC
Category: otc | Type: HUMAN OTC DRUG LABEL
Date: 20240304

ACTIVE INGREDIENTS: POTASSIUM NITRATE 50 mg/1 g; SODIUM FLUORIDE 1.15 mg/1 g
INACTIVE INGREDIENTS: WATER; SORBITOL; HYDRATED SILICA; GLYCERIN; POLYETHYLENE GLYCOL 400; COCAMIDOPROPYL BETAINE; XANTHAN GUM; TITANIUM DIOXIDE; SACCHARIN SODIUM; SODIUM HYDROXIDE

Drug Facts

Active ingredients

Potassium nitrate 5%

Sodium fluoride 0.25% (0.15% w/v fluoride ion)

Purposes

Antihypersensitivity

Anticavity

Uses

- builds increasing protection against painful sensitivity of the teeth to cold, heat, acids, sweets, or contact.
- aids in the prevention of dental cavities.

Warnings

Stop use and ask a dentist if

- the problem persists or worsens. Sensitive teeth may indicate a serious problem that may need prompt care by a dentist.
- pain/sensitivity still persists after 4 weeks of use.

Keep out of reach of children

If more than used for brushing is accidentally swallowed, get medical help or contact a Poison Control Center right away.

Directions

- adults and children 12 years of age and older:
- apply at least a 1-inch strip of the product onto a soft bristle toothbrush.
- brush teeth thoroughly for at least 1 minute twice a day (morning and evening), and not more than 3 times a day, or as recommended by a dentist or doctor. Make sure to brush all sensitive areas of the teeth. Minimize swallowing. Spit out after brushing.
- children under 12 years of age:Consult a dentist or doctor.

Other information

- do not store above 25°C (77°F)

Inactive ingredients

water, sorbitol, hydrated silica, glycerin, PEG-8, flavor, cocamidopropyl betaine, xanthan gum, titanium dioxide, sodium saccharin, sodium hydroxide

Questions or comments?

1-866-844-2797

Additional information

ALWAYS FOLLOW THE LABEL

SENSODYNE PRONAMEL

Acidic foods and drinks can cause enamel loss that can lead to yellowing, dullness and sensitivity. Pronamel has a specialty formulation to help rebuild and restore acid weakened enamel, helping prevent enamel loss for strong, healthy teeth.

ACID ATTACKS ENAMEL

WEAKENING THE ENAMEL STRUCTURE

PRONAMEL REBUILDS & RESTORES ENAMEL

FOR STRONG HEALTHY TEETH

Healthy white teeth start with strong enamel.

Pronamel has a proven specialist technology that has been developed to maximize the effect of fluoride on enamel.

With twice-daily brushing, Pronamel helps to:

• Rebuild enamel strength for strong, healthy teeth

• Protect against the effects of dietary acids

• Relieve sensitive teeth

• Freshen breath

• Protect against cavities

Recycle Carton, Tube and Cap
Save Water

Turn off tap while brushing

Distributed by:

GSK Consumer Healthcare

Warren, NJ 07059

Trademarks are owned by or licensed to the GSK group of companies.

©2022 GSK group of companies or its licensor.

Principal Display Panel

SENSODYNE

PRONAMEL

TOOTHPASTE FOR SENSITIVE TEETH AND CAVITY PREVENTION

Fresh Mint

GENTLE WHITENING

Specialist Enamel Protection

Rebuilds, Restores, Refreshes

NET WT 4.0 OZ (113 g)

62000000079590 Front Carton